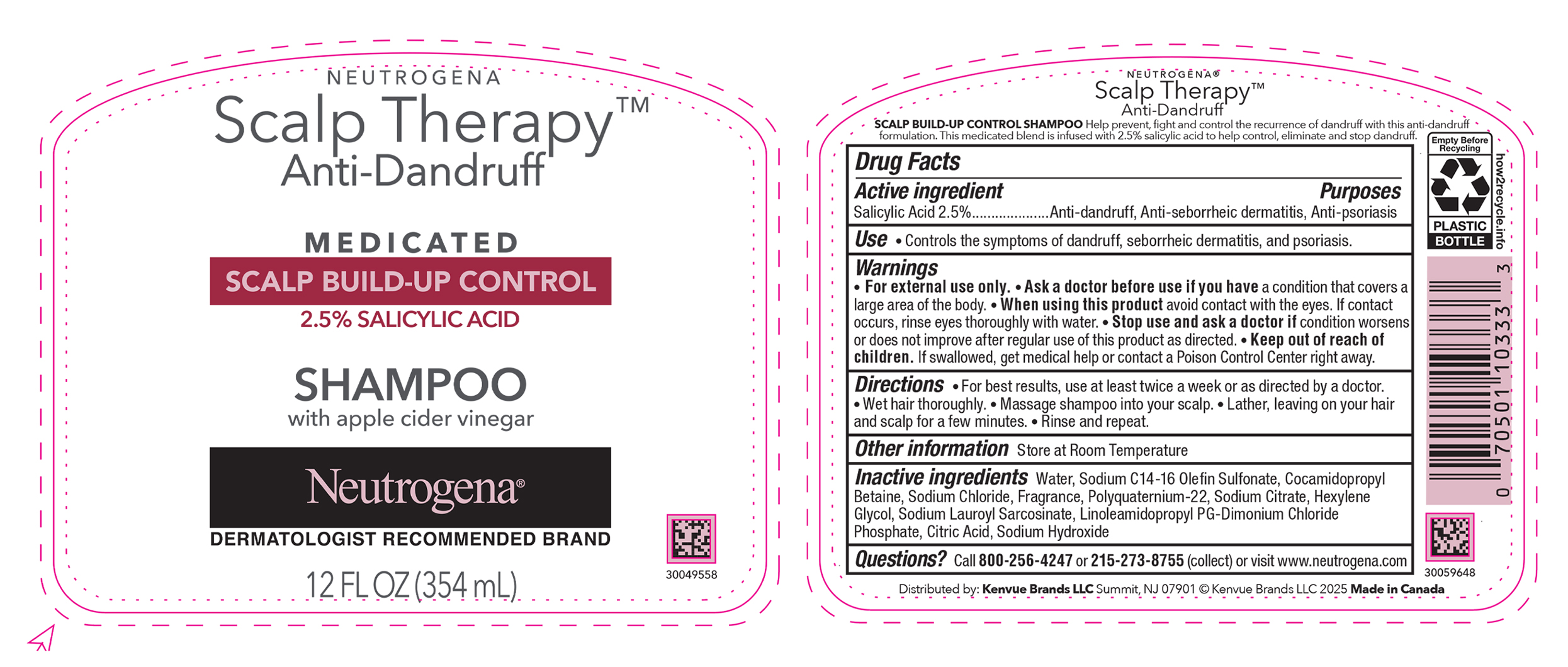 DRUG LABEL: Neutrogena Scalp Therapy Anti-Dandruff Scalp Build-Up Control
NDC: 69968-0724 | Form: SHAMPOO
Manufacturer: Kenvue Brands LLC
Category: otc | Type: HUMAN OTC DRUG LABEL
Date: 20250604

ACTIVE INGREDIENTS: SALICYLIC ACID 25 mg/1 mL
INACTIVE INGREDIENTS: WATER; SODIUM C14-16 OLEFIN SULFONATE; COCAMIDOPROPYL BETAINE; SODIUM CHLORIDE; SODIUM CITRATE, UNSPECIFIED FORM; SODIUM LAUROYL SARCOSINATE; LINOLEAMIDOPROPYL PROPYLENE GLYCOL-DIMONIUM CHLORIDE PHOSPHATE; SODIUM HYDROXIDE; CITRIC ACID MONOHYDRATE; HEXYLENE GLYCOL

NEUTROGENA® Scalp TherapyTM Anti-Dandruff MEDICATED SCALP BUID-UP CONTROL SHAMPOO

Drug Facts

Active ingredient

Salicylic Acid (2.5%)

Purposes

Anti-dandruff, Anti-seborrheic dermatitis, Anti-psoriasis

Use

Controls the symptoms of dandruff, seborrheic dermatitis and psoriasis.

Warnings

For external use only.

Ask a doctor before use if you have a condition that covers a large area of the body.

When using this product avoid contact with the eyes. If contact occurs, rinse eyes thoroughly with water.

Stop use and ask a doctor if condition worsens or does not improve after regular use of this product as directed.

Keep out of reach of children. If swallowed, get medical help or contact a Poison Control Center right away.

Directions

For best results, use at least twice a week or as directed by a doctor.

- Wet hair thoroughly.
- Massage shampoo into the scalp.
- Lather, leaving on your hair and scalp for a few minutes.
- Rinse and repeat.

Other information

Store at room temperature.

Inactive ingredients

Water, Sodium C14-16 Olefin Sulfonate, Cocamidopropyl Betaine, Sodium Chloride, Polyquaternium-22, Sodium Citrate, Hexylene Glycol, Sodium Lauroyl Sarcosinate, , Linoleamidopropyl PG-Dimonium Chloride Phosphate, Citric Acid, Sodium Hydroxide

Questions?

Call 800-256-4247or 215-273-8755 (collect) or visit www.neutrogena.com

Distributed by:
Kenvue Brands LLC
Summit, NJ 07901

PRINCIPAL DISPLAY PANEL - 354 mL Bottle Carton

NEUTROGENA

Scalp TherapyTM

Anti-Dandruff

MEDICATED

SCALP BUID-UP CONTROL

2.5% SALICYLIC ACID

SHAMPOO

with apple cider vinegar

Neutrogena®

DERMATOLOGIST RECOMMENDED BRAND

12 FL OZ (354 mL)